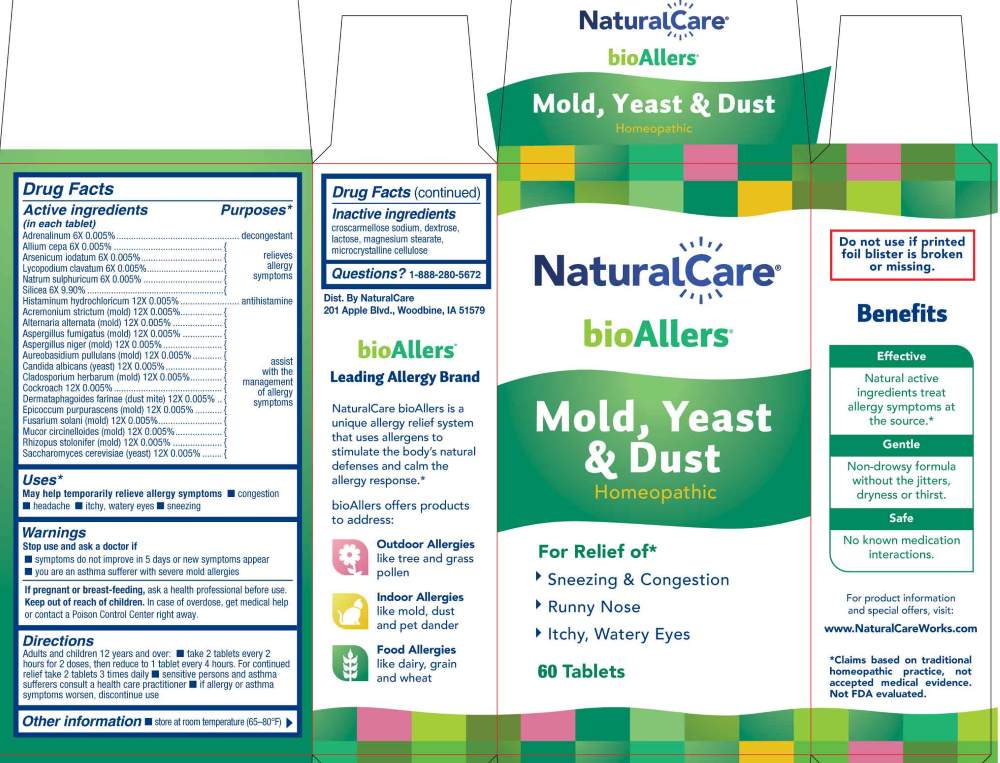 DRUG LABEL: Mold, Yeast and Dust
NDC: 70163-0009 | Form: TABLET
Manufacturer: NaturalCare
Category: homeopathic | Type: HUMAN OTC DRUG LABEL
Date: 20260203

ACTIVE INGREDIENTS: SAROCLADIUM STRICTUM 12 [hp_X]/1 1; EPINEPHRINE 6 [hp_X]/1 1; ONION 6 [hp_X]/1 1; ALTERNARIA ALTERNATA 12 [hp_X]/1 1; ARSENIC TRIIODIDE 6 [hp_X]/1 1; ASPERGILLUS FUMIGATUS 12 [hp_X]/1 1; ASPERGILLUS NIGER VAR. NIGER 12 [hp_X]/1 1; AUREOBASIDIUM PULLULANS VAR. PULLUTANS 12 [hp_X]/1 1; CANDIDA ALBICANS 12 [hp_X]/1 1; CLADOSPORIUM HERBARUM 12 [hp_X]/1 1; PERIPLANETA AMERICANA 12 [hp_X]/1 1; DERMATOPHAGOIDES FARINAE 12 [hp_X]/1 1; EPICOCCUM NIGRUM 12 [hp_X]/1 1; HAEMATONECTRIA HAEMATOCOCCA 12 [hp_X]/1 1; HISTAMINE DIHYDROCHLORIDE 12 [hp_X]/1 1; LYCOPODIUM CLAVATUM SPORE 6 [hp_X]/1 1; MUCOR CIRCINELLOIDES 12 [hp_X]/1 1; SODIUM SULFATE 6 [hp_X]/1 1; RHIZOPUS STOLONIFER 12 [hp_X]/1 1; SACCHAROMYCES CEREVISIAE 12 [hp_X]/1 1; SILICON DIOXIDE 6 [hp_X]/1 1
INACTIVE INGREDIENTS: CROSCARMELLOSE SODIUM; DEXTROSE, UNSPECIFIED FORM; LACTOSE MONOHYDRATE; MAGNESIUM STEARATE; MICROCRYSTALLINE CELLULOSE

DRUG FACTS:

ACTIVE INGREDIENT:

(in each tablet) Adrenalinum 6X 0.005%, Allium Cepa 6X 0.005%, Arsenicum Iodatum 6X 0.005%, Lycopodium Clavatum 6X 0.005%, Natrum Sulphuricum 6X 0.005%, Silicea 6X 9.90%, Histaminum Hydrochloricum 12X 0.005%, Acremonium Strictum 12X 0.005%, Alternaria Alternata (mold) 12X 0.005%, Aspergillus Fumigatus (mold) 12X 0.005%, Aspergillus Niger (mold) 12X 0.005%, Aureobasidium Pullulans (mold) 12X 0.005%, Candida Albicans (yeast) 12X 0.005%, Cladosporium Herbarum (mold) 12X 0.005%, Cockroach 12X 0.005%, Dermatophagoides Farinae (dust mite) 12X 0.005%, Epicoccum Purpurascens (mold) 12X 0.005%, Fusarium Solani (mold) 12X 0.005%, Mucor Circinelloides (mold) 12X 0.005%, Rhizopus Stolonifer (mold) 12X 0.005%, Saccharomyces Cerevisiae (yeast) 12X 0.005%.

PURPOSE:

Adrenalinum - decongestant, Allium Cepa – relieves allergy symptoms, Arsenicum Iodatum - relieves allergy symptoms, Lycopodium Clavatum - relieves allergy symptoms, Natrum Sulphuricum - relieves allergy symptoms, Silicea - relieves allergy symptoms, Histaminum Hydrochloricum - antihistamine, Acremonium Strictum – assist with the management of allergy symptoms, Alternaria Alternata - assist with the management of allergy symptoms, Aspergillus Fumigatus - assist with the management of allergy symptoms, Aspergillus Niger - assist with the management of allergy symptoms, Aureobasidium Pullulans - assist with the management of allergy symptoms, Candida Albicans - assist with the management of allergy symptoms, Cladosporium Herbarum - assist with the management of allergy symptoms, Cockroach - assist with the management of allergy symptoms, Dermatophagoides Farinae - assist with the management of allergy symptoms, Epicoccum Purpurascens - assist with the management of allergy symptoms, Fusarium Solani - assist with the management of allergy symptoms, Mucor Circinelloides - assist with the management of allergy symptoms, Rhizopus Stolonifer - assist with the management of allergy symptoms, Saccharomyces Cerevisiae - assist with the management of allergy symptoms*
*Claims based on traditional homeopathic practice, not accepted medical evidence. Not FDA evaluated.

USES:

May help temporarily relieve allergy symptoms

■ headache ■ itchy, watery eyes ■ sneezing*

*Claims based on traditional homeopathic practice, not accepted medical evidence. Not FDA evaluated.

WARNINGS:

Stop use and ask a doctor if

■ symptoms do not improve in 5 days or new symptoms appear

■ you are an asthma sufferer with severe mold allergies

If pregnant or breast-feeding, ask a health professional before use.

Keep out of reach of children. In case of overdose, get medical help or contact a Poison Control Center right away.

Do not use if printed foil blister is broken or missing.

■ Store at room temperature (65-80ºF)

KEEP OUT OF REACH OF CHILDREN:

In case of overdose, get medical help or contact a Poison Control Center right away.

DIRECTIONS:

Adults and children 12 years and over:

■ take 2 tablets every 2 hours for 2 doses, then reduce to 1 tablet every 4 hours. For continued relief take 2 tablets 3 times daily

■ sensitive persons and asthma sufferers consult a health care practitioner

■ if allergy or asthma symptoms worsen, discontinue use

INACTIVE INGREDIENTS:

croscarmellose sodium, dextrose, lactose, magnesium stearate, microcrystalline cellulose

QUESTIONS:

Dist. By NaturalCare

201 Apple Blvd.

Woodbine, IA 51579

www.NaturalCareWorks.com

1-888-280-5672

PACKAGE LABEL DISPLAY:

NaturalCare

bioAllers

Mold, Yeast & Dust

Homeopathic

For Relief of*

Sneezing & Congestion

Runny Nose

Itchy, Watery Eyes

60 Tablets